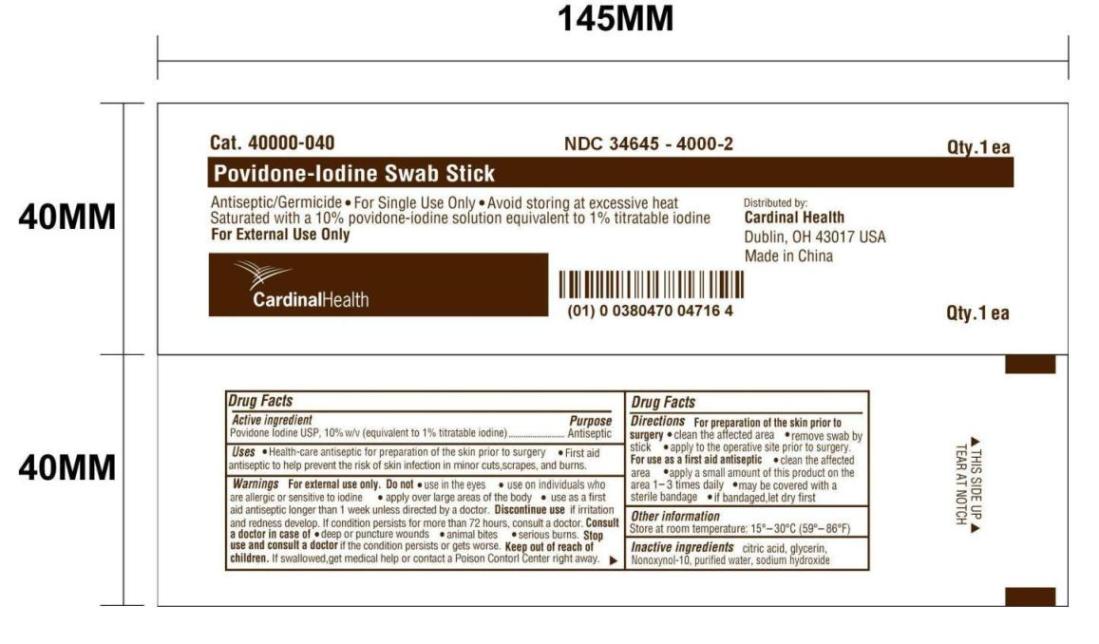 DRUG LABEL: Povidone-Iodine
NDC: 34645-4000 | Form: SWAB
Manufacturer: Jiangsu Province JianErKang Medical Dressing Co. ,Ltd.
Category: otc | Type: HUMAN OTC DRUG LABEL
Date: 20100101

ACTIVE INGREDIENTS: POVIDONE-IODINE 0.1 mL/1 mL

Drug Facts

PACKAGE LABEL

Cat.40000-040 NDC 34645-4000-2 Qty. 1ea

Povidone-Iodine Swab Stick

Antiseptic/Germicide * For Single Use Only * Avoid storing at excessive heat

Saturated with a 10% povidone-iodine solution equivalent to 1% titratable iodine

For External Use Only

Distributed by:

Cardinal Health

Dublin, OH 43017 USA

Made in China

Active ingredient

Povidone Iodine USP, 10% w/v

(equivalent to 1% titratable iodine)

Purpose

Antiseptic

Uses

Health-care antiseptic for preparation of the skin prior to surgery

First aid antiseptic to help prevent the risk of skin infection in minor cuts, scrapes, and burns.

Warnings

For external use only.

Do not * use in the eyes * use on individuals who are allergic or sensitive to iodine

* apply over large areas of the body * use as a first aid antiseptic longer than 1 week unless directed by a doctor.

Discontinue use
If irritation and redness develop. If condition persists for more than 71 hours, consult a doctor.

Consult a doctor in case of
* deep or puncture wounds * animal bites * serious burns.

Directions
Clean the affected area
Apply product on the area 1-3 times daily and discard
May be covered with a sterile bandage when dry

Stop use and consult a doctor
if the condition persists or gets worse.

Keep out of reach of children.
If swallowed, get medical help or contact a Poison Control Center right away.

Directions
For preparation of the skin prior to surgery
* clean the affected area
* remove swab by stick
* apply to the operative site prior to surgery
For use as a first aid antiseptic
* clean the affected area
* apply a small amount of this product on the area 1-3 times daily
* may be covered with a sterile bandage
* if bandaged, let dry first

Other information
Store at room temperature: 15o - 30o C (59o-86o F)

Inactive ingredients

aitric acid, glycerin, Nonoxynol-10, purified water, sodium hydroxide

Image of Pouch Label